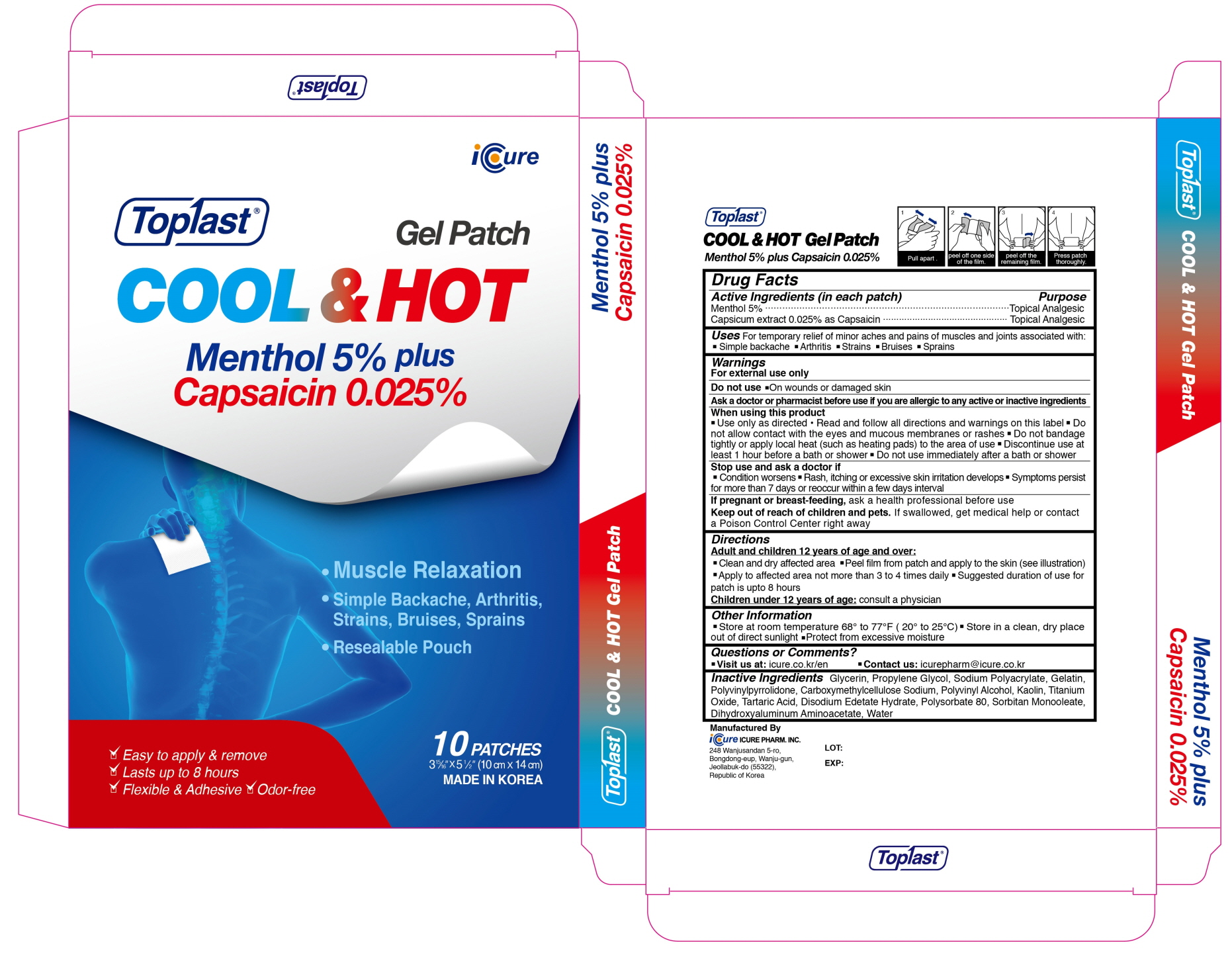 DRUG LABEL: Toplast Cool and Hot Menthol 5percent plus Capsaicin 0.025percent
NDC: 73279-0018 | Form: PATCH
Manufacturer: Icure Pharmaceutical Inc, Wanju Factory
Category: otc | Type: HUMAN OTC DRUG LABEL
Date: 20200728

ACTIVE INGREDIENTS: Menthol 350 mg/1 1; Capsaicin 1.75 mg/1 1
INACTIVE INGREDIENTS: Glycerin; Propylene Glycol; Gelatin; CARBOXYMETHYLCELLULOSE SODIUM, UNSPECIFIED; Kaolin; TITANIUM DIOXIDE; Tartaric Acid; EDETATE DISODIUM; Polysorbate 80; SORBITAN MONOOLEATE; Dihydroxyaluminum Aminoacetate; Water

Drug Facts

ACTIVE INGREDIENTS

Menthol 5%
Capsicum extract 0.025% as Capsaicin

INACTIVE INGREDIENTS

Glycerin, Propylene Glycol, Sodium Polyacrylate, Gelatin, Polyvinylpyrrolidone, Carboxymethylcellulose Sodium, Polyvinyl Alcohol, Kaolin, Titanium Oxide, Tartaric Acid, Disodium Edetate Hydrate, Polysorbate 80, Sorbitan Monooleate, Dihydroxyaluminum Aminoacetate, Water

PURPOSE

Topical Analgesic

WARNINGS

For external use only
--------------------------------------------------------------------------------------------------------
Do not use
■ On wounds or damaged skin
--------------------------------------------------------------------------------------------------------
Ask a doctor or pharmacist before use if you are allergic to any active or inactive ingredients
--------------------------------------------------------------------------------------------------------
When using this product
■ Use only as directed ■ Read and follow all directions and warnings on this label ■ Do not allow contact with the eyes and mucous membranes or rashes ■ Do not bandage tightly or apply local heat (such as heating pads) to the area of use ■ Discontinue use at least 1 hour before a bath or shower ■ Do not use immediately after a bath or shower
--------------------------------------------------------------------------------------------------------
Stop use and ask a doctor if
■ Condition worsens ■ Rash, itching or excessive skin irritation develops ■ Symptoms persist for more than 7 days or reoccur within a few days interval
--------------------------------------------------------------------------------------------------------
If pregnant or breast-feeding, ask a health professional before use

Keep out of reach of children and pets

If swallowed, get medical help or contact a Poison Control Center right away

Uses

For temporary relief of minor aches and pains of muscles and joints associated with : ■ Simple backache ■ Arthritis ■ Strains ■ Bruises ■ Sprains

Directions

Adult and children 12 years of age and over :
■ Clean and dry affected area ■ Peel film from patch and apply to the skin (see illustration) ■ Apply to affected area not more than 3 to 4 times daily ■ Suggested duration of use for patch is upto 8 hours
Children under 12 years of age : Consult a physician

Other Information

■ Store at room temperature 68° to 77°F (20° to 25°C) ■ Store in a clean, dry place out of direct sunlight ■ Protect from excessive moisture

Questions or Comments

■ Visit us at : icure.co.kr/en ■ Contact us : icurepharm@icure.co.kr